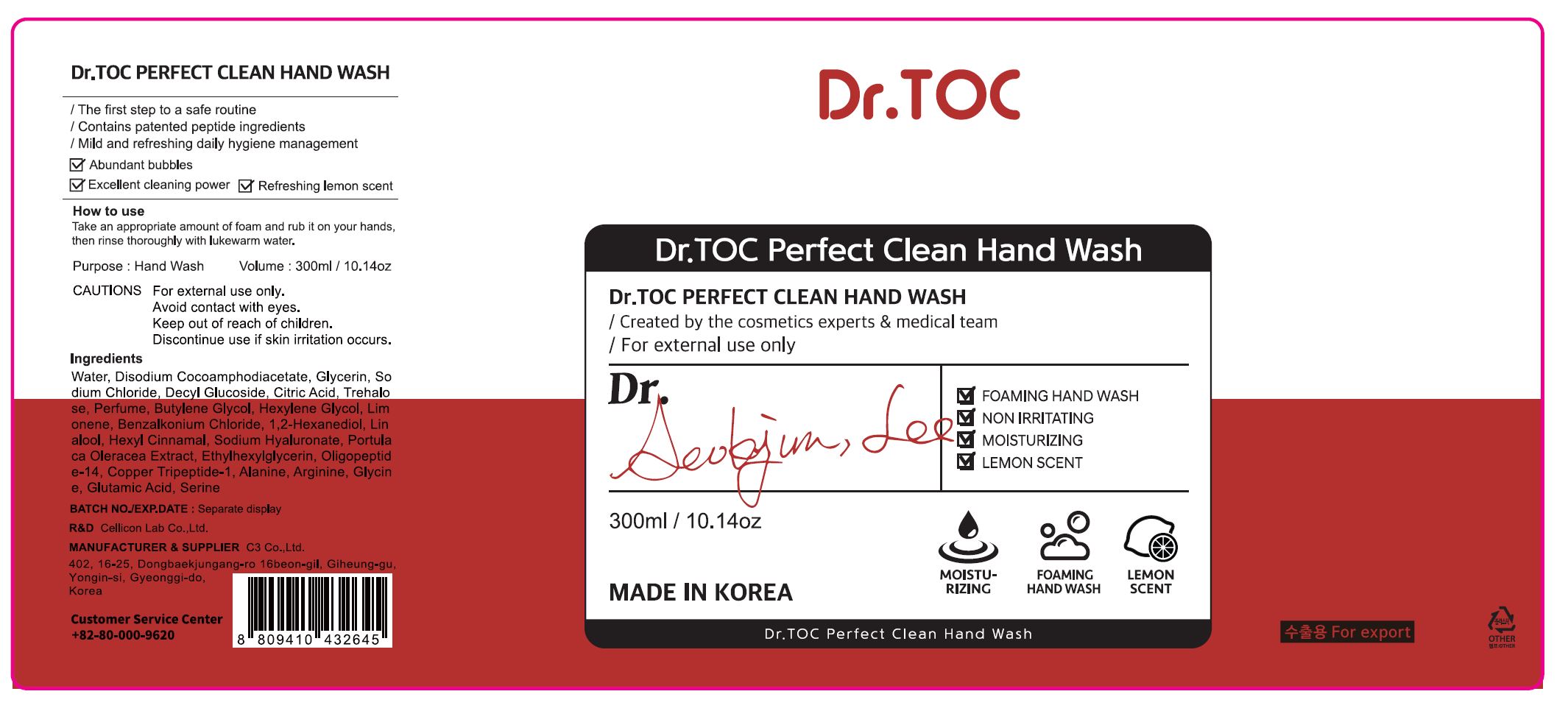 DRUG LABEL: Dr.TOC PERFECT CLEAN HAND WASH
NDC: 70818-026 | Form: LIQUID
Manufacturer: C3 Co., Ltd.
Category: otc | Type: HUMAN OTC DRUG LABEL
Date: 20210214

ACTIVE INGREDIENTS: BENZALKONIUM CHLORIDE 0.05 g/100 mL
INACTIVE INGREDIENTS: WATER

C3 Co., Ltd. - isLeaf Hand Cleaning Gel

ACTIVE INGREDIENT

Benzalkonium Chloride

INACTIVE INGREDIENT

Water
Disodium Cocoamphodiacetate
Glycerin
Sodium Chloride
Decyl Glucoside
Citric acid
Fragrance
Trehalose
Butylene Glycol
Hexylene glycol
Limonene
1,2-Hexanediol
Linalool
Hexyl Cinnamal
Sodium Hyaluronate
Portulaca Oleracea Extract
Ethylhexylglycerin
Coppertripeptide-1
Oligopeptide-14
Alanine
Arginine
Glycine
Glutamic Acid
Serine

PURPOSE

Antiseptic

keep out of reach of the children

INDICATIONS AND USAGE

Take an appropriate amount of foam and rub it on your hands,
then rinse thoroughly with lukewarm water.

WARNINGS

For external use only.

Avoid contact with eyes.

Keep out of reach of children.

Discontinue use if skin irritation occurs.

DOSAGE AND ADMINISTRATION

for external use only